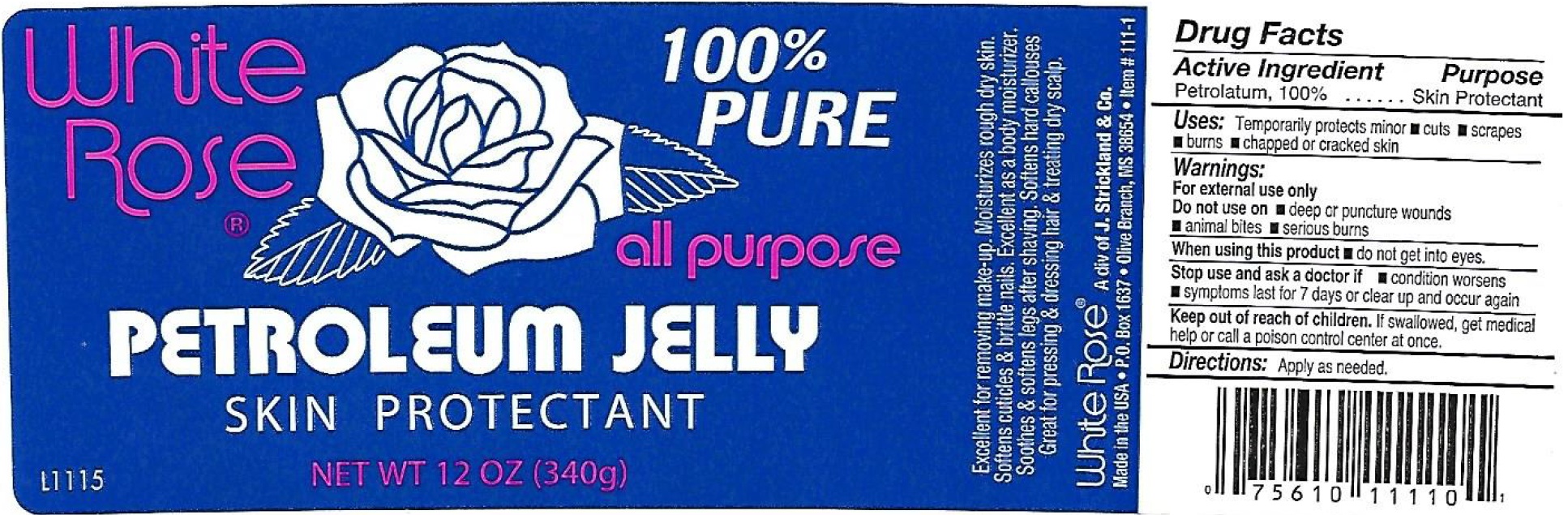 DRUG LABEL: White Rose Petroleum Jelly
NDC: 12022-031 | Form: OINTMENT
Manufacturer: J. Strickland & Co.
Category: otc | Type: HUMAN OTC DRUG LABEL
Date: 20231021

ACTIVE INGREDIENTS: PETROLATUM 1000 mg/1 g
INACTIVE INGREDIENTS: WATER

White Rose Petroleum Jelly

Active Ingredient

Petrolatum, 100%

Purpose

Skin Protectant

Uses:

Temporarily protects minor

- cuts
- scrapes
- burns
- cahpped or cracked skin

Warnings:

For external use only

Do not use on

- deep or puncture woods
- animal bites
- serious burns

When using this product

- do not get into eyes.

Stop use and ask a doctor if

- condition worsens
- symptoms last for 7 days or clear up and occur again

Keep out of reach of children

If swallowed, get medical help or call a poison control center at once.

Directions:

Apply as needed.

Inactive Ingredient

water